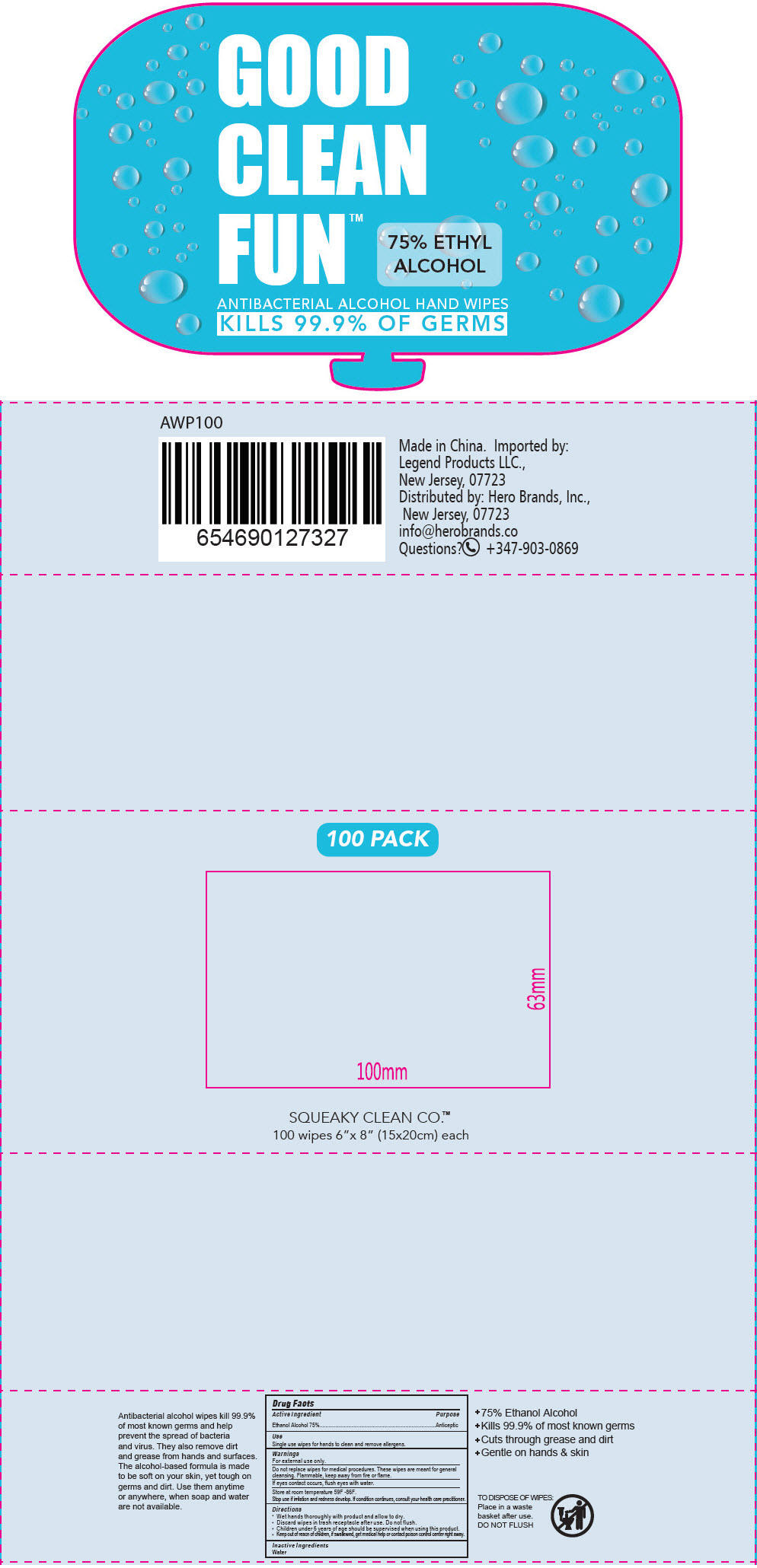 DRUG LABEL: Squeaky Clean Alcohol Hand Wipes
NDC: 90114-202 | Form: CLOTH
Manufacturer: Hero Brands, Inc.
Category: otc | Type: HUMAN OTC DRUG LABEL
Date: 20200807

ACTIVE INGREDIENTS: Alcohol 75 mL/100 mL
INACTIVE INGREDIENTS: Water

Squeaky Clean Alcohol Hand Wipes

Drug Facts

Active Ingredient

Ethanol Alcohol 75%

Purpose

Anticeptic

Use

Single use wipes for hands to clean and remove allergens.

Warnings

For external use only.

WHEN USING

Do not replace wipes for medical procedures. These wipes are meant for general cleansing. Flammable, keep away from fire or flame.

If eyes contact occurs, flush eyes with water.

STORAGE AND HANDLING

Store at room temperature 59F -86F.

Stop use if irritation and redness develop. If condition continues, consult your health care practitioner.

Directions

- Wet hands thoroughly with product and allow to dry.
- Discard wipes in trash receptacle after use. Do not flush.
- Children under 6 years of age should be supervised when using this product.

KEEP OUT OF REACH OF CHILDREN

- Keep out of reacn of children, if swallewed, get medical help or contact poison control center right away.

Inactive Ingredients

Water

Questions?

+347-903-0869

Distributed by: Hero Brands, Inc.,
New Jersey, 07723

PRINCIPAL DISPLAY PANEL - 100 Wipe Bag

GOOD
CLEAN
FUN™

75% ETHYL
ALCOHOL

ANTIBACTERIAL ALCOHOL HAND WIPES

KILLS 99.9% OF GERMS